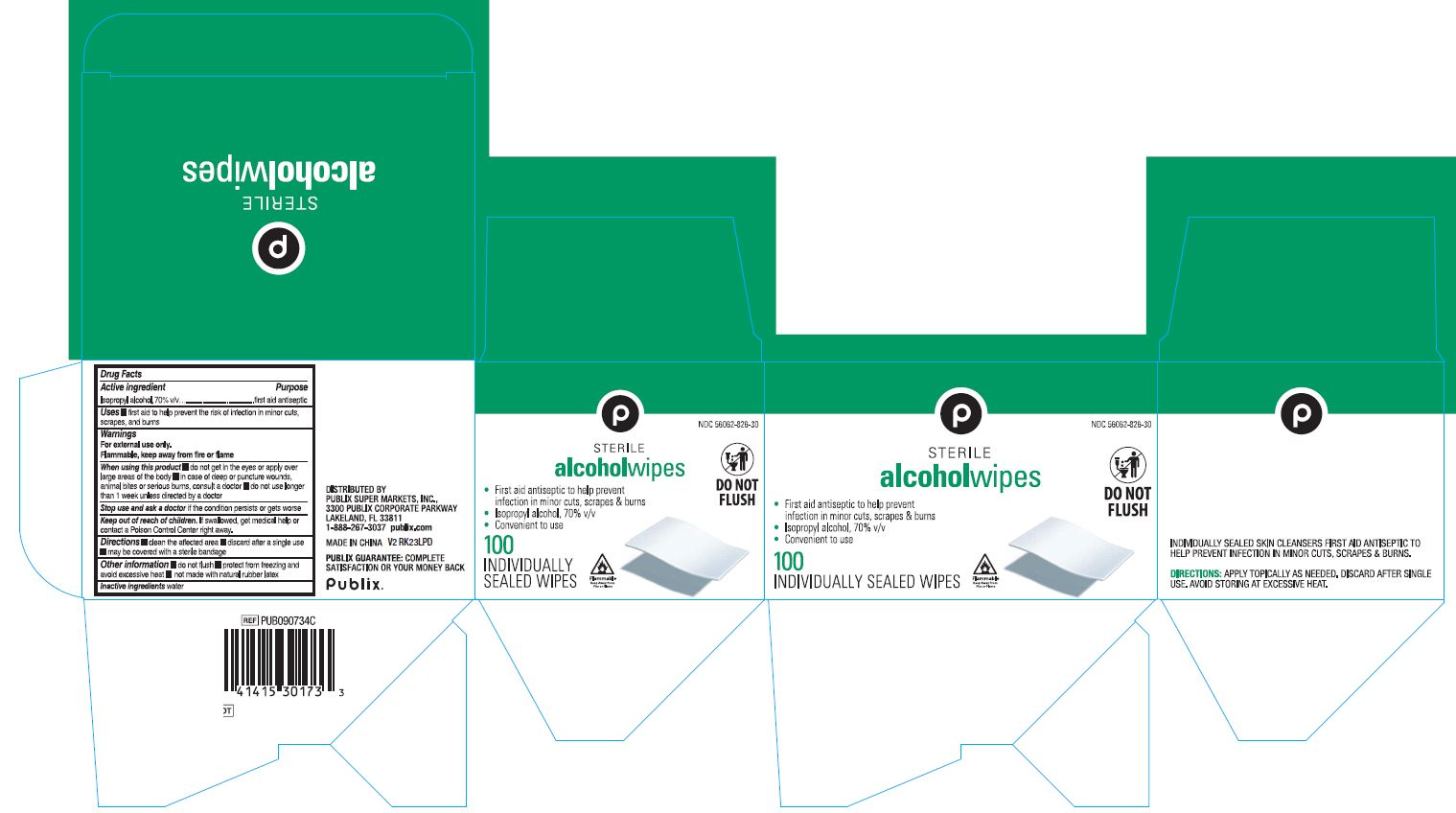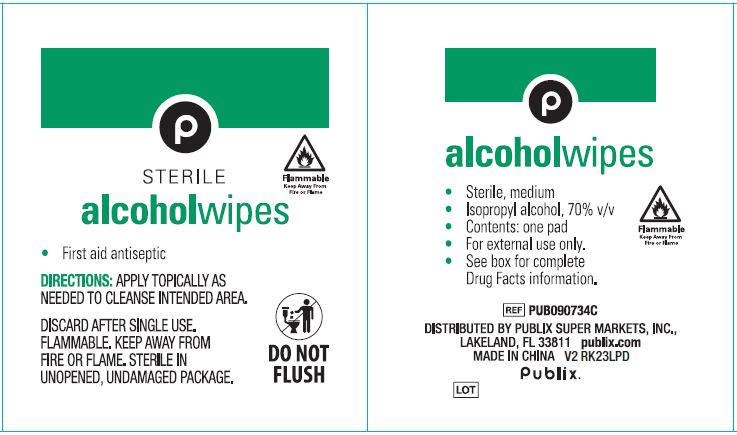 DRUG LABEL: Publix Alcohol
NDC: 56062-826 | Form: SWAB
Manufacturer: Publix Super Markets, Inc.
Category: otc | Type: HUMAN OTC DRUG LABEL
Date: 20250103

ACTIVE INGREDIENTS: ISOPROPYL ALCOHOL 70 mL/100 mL
INACTIVE INGREDIENTS: WATER

56062-826 Publix IPA prep pad

Active ingredient

Isopropyl alcohol 70% v/v

Purpose

first aid antiseptic

Uses

- first aid to help prevent the risk of infection in minor cuts, scrapes and burns

Warnings

- For external use only.
- Flammable, keep away from fire or flame.

Do not use

- • with electrocautery procedures
- • longer than 1 week unless directed by a doctor

When using this product

- • do not get into eyes
- • do not apply over large areas of the body
- • in case of deep or puncture wounds, animal bites or serious burns, consult a doctor

Stop use and ask a doctor if

- • irritation and redness develop
- • condition gets worse or persists for more than 72 hours

Keep out of reach of children.

If accidentally swallowed, get medical help or contact a Poison Control Center right away.

Directions

- clean the affected area
- discard after single use
- may be covered with a sterile bandage

Other information

- do not flush
- protect from freezing and avoid excessive heat
- not made with natural rubber latex

Inactive ingredients

water

Manufacturing Information

Distributed by:

Publix Super Markets, Inc.

Publix Corporate Pkwy, Lakeland, FL 33811 USA

Made in China

publix.com

REF: PUB090734C

V2 RK23LPD